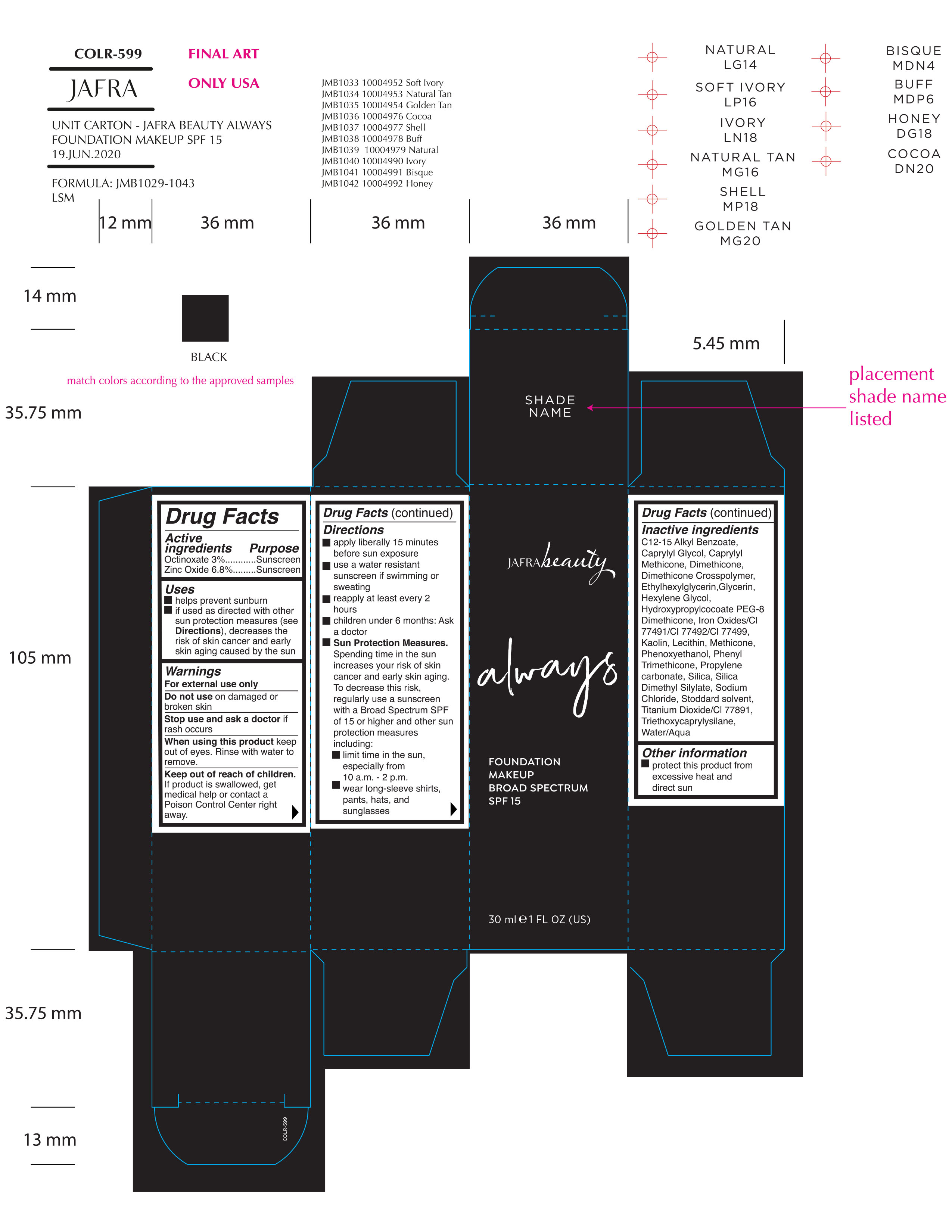 DRUG LABEL: Always Foundation Makeup Broad Spectrum SPF 15 Honey
NDC: 68828-420 | Form: CREAM
Manufacturer: Jafra Cosmetics International
Category: otc | Type: HUMAN OTC DRUG LABEL
Date: 20200717

ACTIVE INGREDIENTS: ZINC OXIDE 6.8 g/100 mL; OCTINOXATE 3 g/100 mL
INACTIVE INGREDIENTS: METHICONE (20 CST); SILICA DIMETHYL SILYLATE; WHITE SPIRIT TYPE 1; FERRIC OXIDE YELLOW; ALKYL (C12-15) BENZOATE; CAPRYLYL TRISILOXANE; GLYCERIN; HEXYLENE GLYCOL; CAPRYLYL GLYCOL; TRIETHOXYCAPRYLYLSILANE; SODIUM CHLORIDE; TITANIUM DIOXIDE; HYDROXYPROPYLCOCOATE PEG-8 DIMETHICONE; FERROSOFERRIC OXIDE; KAOLIN; LECITHIN, SOYBEAN; PHENOXYETHANOL; PHENYL TRIMETHICONE; PROPYLENE CARBONATE; WATER; SILICON DIOXIDE; FERRIC OXIDE RED; DIMETHICONE; DIMETHICONE CROSSPOLYMER (450000 MPA.S AT 12% IN CYCLOPENTASILOXANE); ETHYLHEXYLGLYCERIN

Always Foundation Makeup Broad Spectrum SPF 15 Honey

Active Ingredients Purpose

Octinoxate 3% Sunscreen

Zinc Oxide 6.8% Sunscreen

Uses

Helps Prevent Sunburn
If used as directed with other sun protection measures (see Directions), decreases the risk of skin cancer and early skin aging caused by the sun.

Keep out of reach of children

If product is swallowed, get medical help or contact a poison Control Center right away

Stop use and ask a doctor if rash occurs

Warnings

For external use only
Do not use on damaged or broken skin
When using this product keep out of eyes. Rinse with water to remove

Directions

Apply liberally 15 minutes before sun exposure
Use a water resistant sunscreen if swimming or sweating
Reapply at least every 2 hours.
Sun Protection Measures Spending time in the sun increases your risk of skin cancer and early skin aging. To decrease this risk, regularly use a sunscreen with a Broad-Spectrum SPF value of 15 or higher and other sun
protection measures including:

• limit your time in the sun, especially from 10
a.m. – 2 p.m. • wear long-sleeved shirts, pants, hats, and sunglasses

• Children under 6 months of age: ask a doctor.

Inactive ingredients

C12-15 Alkyl Benzoate, Caprylyl Glycol, Caprylyl Methicone, Dimethicone, Dimethicone Crosspolymer, Ethylhexylglycerin, Glycerin, Hexylene Glycol, Hydroxypropylcocoate PEG-8 Dimethicone, Iron Oxides/CI 77491/CI 77492/CI 77499, Kaolin, Lecithin, Methicone, Phenoxyethanol, Phenyl Trimethicone, Propylene carbonate, Silica, Silica Dimethyl Silylate, Sodium Chloride, Stoddard solvent, Titanium Dioxide/CI 77891, Triethoxycaprylysilane, Water/Aqua

PACKAGE LABEL

Jafra beauty

always

Foundation Makeup Broad Spectrum SPF 15 Honey

30 ml 1 FL OZ (US)